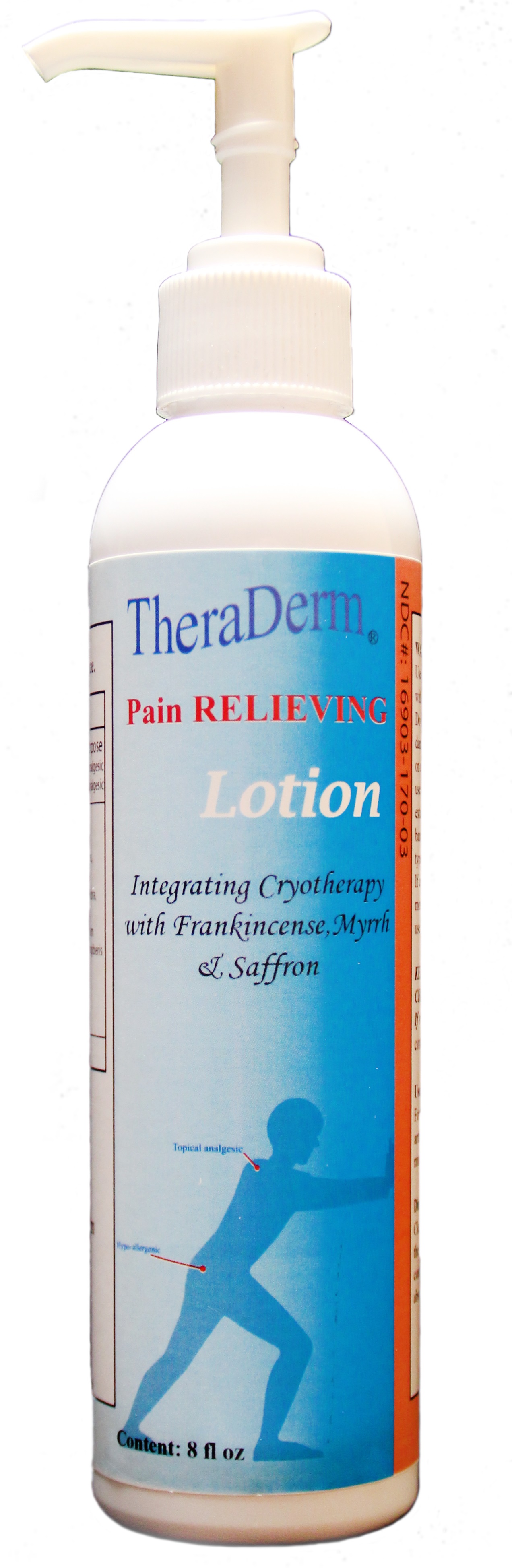 DRUG LABEL: Thera Derm
NDC: 16903-170 | Form: LOTION
Manufacturer: Manna Omni International Incorporated
Category: otc | Type: HUMAN OTC DRUG LABEL
Date: 20180219

ACTIVE INGREDIENTS: CAMPHOR LEAF OIL 6 mg/240 mg; 7-AMINODESACETOXYCEPHALOSPORANIC ACID 450 mg/240 mg; MENTHOL, UNSPECIFIED FORM 13 mg/240 mg; METHYL SALICYLATE 2-ETHYLBUTYRATE 28 mg/240 mg; PEPPERMINT OIL 13 mg/240 mg
INACTIVE INGREDIENTS: PAEONIA LACTIFLORA FLOWER 4 mg/240 mg; SALVIA MILTIORRHIZA ROOT 4 mg/240 mg; ANGELICA SINENSIS ROOT OIL 4 mg/240 mg; LIGUSTICUM SINENSE SUBSP. CHUANXIONG ROOT 4 mg/240 mg; 12-HYDROXYSTEARIC ACID 15 mg/240 mg; MYRRH OIL 4 mg/240 mg; LAVENDER OIL 3 mg/240 mg; PERSICARIA FILIFORMIS FLOWERING TOP 4 mg/240 mg; NOTOPTERYGIUM INCISUM ROOT 4 mg/240 mg; ANGELICA PUBESCENS ROOT 4 mg/240 mg; ZINGIBER CASSUMUNAR ROOT OIL 4 mg/240 mg; COCONUT OIL 4 mg/240 mg; ALOE 7.5 mg/240 mg; CARTHAMUS TINCTORIUS FLOWER OIL 4 mg/240 mg; FRANKINCENSE OIL 4 mg/240 mg

Thera Derm Pain Relieving Lotion

Directions:

For the temporary relief of minor arthritis pain, simple backache, muscle strains and sprains.

Clean affected Area and rub or massage area continuously until lotion has been absoprbed into the area.

INSTRUCTIONS FOR USE

Directions: clean the affected area, then apply to pain area. Rub or massage the area continuously until the lotion has been fully absorbed into the area.

Warning: for external use only

Use only as directed. Avoid contact with the eyes and mucous membranes. DO not apply to open wounds, damaged or very sensitive skin. Test on a small area before use. Do not use in combination with other external analgesic products. Do not bandage tightly or cover with any type of wrap, except clothing. If condition worsens, or persists for more than seven days, discontinue use and consult a physician.

KEEP OUT OF THE REACH OF CHILDREN

If swallowed, get medical help or contact Poison Control right away.

Active Ingredients:

Menthol, Methyl Salicylate, Peppermint Oil, Camphor.

Inactive Ingredients

Salvia Miltiorrhiza root, Carthamus Tinctorius Flower Oil, Lavender Oil, Angelica Actiloba Flowering Top, Aloe,Zingiber Cassumunar Root Oil,Angelicae Pubescens Root,Stearic Acid, Prunus Persica Flower Bud,Notopterygium Franchetii Root,Frankincense Oil, Ligusticum Sinese Subsc, Chuanxiong Root, Myrrh,nGlycerin, Vitamin E Oil,Coconut Oil.

Purpose

The Purpose of our pain relieving Lotion is to provide temporary relief of minor aches and pains, arthritiis pain, backache, muscle aches and strains.

Indications and Usage

For the temporary relief of minor aches and pains, arthritis pain, backache,muscle vstrains and sprains. Make sure to clean the affected area then apply lotion and rub into the skin until it absorbs.